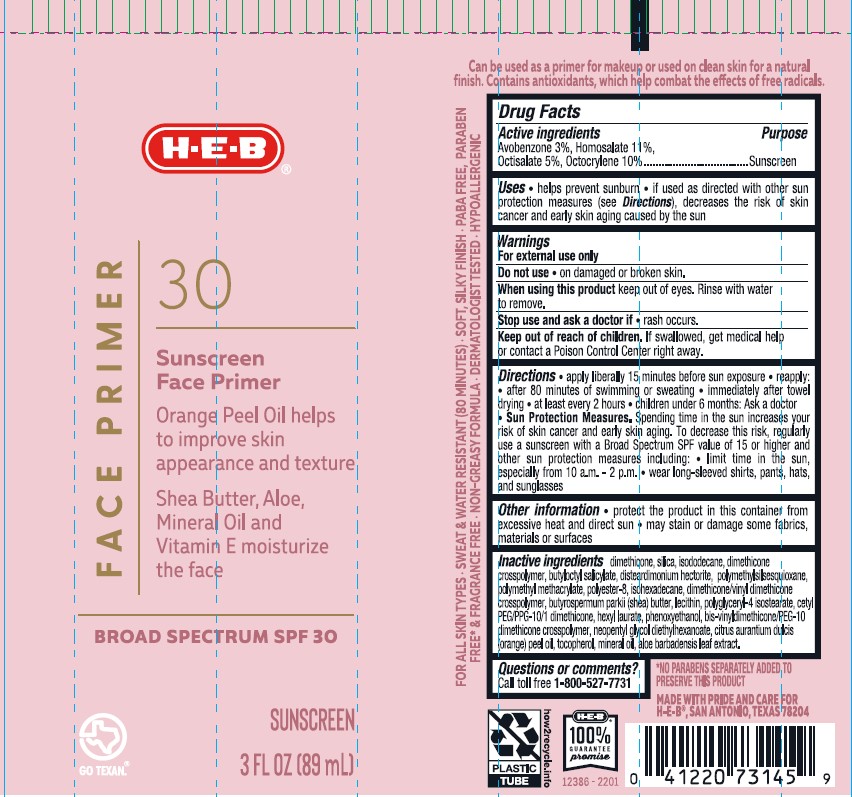 DRUG LABEL: HEB Face Primer 30 Sunscreen Face Primer SPF 30
NDC: 37808-150 | Form: LOTION
Manufacturer: H-E-B
Category: otc | Type: HUMAN OTC DRUG LABEL
Date: 20241015

ACTIVE INGREDIENTS: HOMOSALATE 110 mg/1 mL; AVOBENZONE 30 mg/1 mL; OCTISALATE 50 mg/1 mL; OCTOCRYLENE 100 mg/1 mL
INACTIVE INGREDIENTS: DIMETHICONE/VINYL DIMETHICONE CROSSPOLYMER (SOFT PARTICLE); ISOHEXADECANE; MINERAL OIL; ORANGE OIL; DIMETHICONE/DIENE DIMETHICONE CROSSPOLYMER; POLY(METHYL METHACRYLATE; 450000 MW); PHENOXYETHANOL; SHEA BUTTER; ISODODECANE; POLYESTER-8 (1400 MW, CYANODIPHENYLPROPENOYL CAPPED); POLYGLYCERYL-4 ISOSTEARATE; LECITHIN, SOYBEAN; POLYMETHYLSILSESQUIOXANE (4.5 MICRONS); .ALPHA.-TOCOPHEROL, DL-; SILICON DIOXIDE; ALOE VERA LEAF; BUTYLOCTYL SALICYLATE; DISTEARDIMONIUM HECTORITE; HEXYL LAURATE; NEOPENTYL GLYCOL DIETHYLHEXANOATE; CETYL PEG/PPG-10/1 DIMETHICONE (HLB 5)

HEB Face Primer 30 Sunscreen Face Primer SPF 30 Lotion

Active ingredients

Avobenzone 3.0%, Homosalate 11.0%, Octisalate 5.0%, Octocrylene 10.0%

Purpose

Sunscreen

Uses

- Helps prevent sunburn
- If used as directed with other sun protection measures (see Directions), decreases the risk of skin cancer and early aging caused by the sun

Warnings

For external use only

Do not use

• on damaged or broken skin.

When using this product

keep out of eyes. Rinse with water to remove.

Stop use and ask a doctor if

• rash occurs.

Keep out of reach of children.

If swallowed, get medical help or contact a Poison Control Center right away.

Directions

- apply liberally 15 minutes before sun exposure.
- reapply:
- after 80 minutes of swimming or sweating
- immediately after towel drying
- at least every 2 hours
- children under 6 months of age: Ask a doctor
- Sun Protection Measures. Spending time in the sun increases your risk of skin cancer and early skin aging. To decrease this risk, regularly use a sunscreen with a Broad Spectrum SPF value of 15 or higher and other sun protection measures including:
- limit time in the sun especially from 10 a.m. – 2 p.m.
- wear long-sleeved shirts, pants, hats, and sunglasses

Other information

- protect the product in this container from excessive heat and direct sun
- may stain or damage some fabrics, materials or surfaces

Inactive ingredients

aloe barbadensis leaf extract, Bis-vinyldimethicone/peg-10 dimethicone crosspolymer, butyloctyl salicylate, butyrospermum parkii (shea) butter, cetyl peg/ppg-10/1 dimethicone, citrus aurantium dulcis (orange) oil, dimethicone, dimethicone crosspolymer, dimethicone/vinyl dimethicone crosspolymer, disteardimonium hectorite, hexyl laurate, hydrated silica, isododecane, isohexadecane, lecithine, mineral oil, neopentyl glycol diethylhexanoate, phenoxyethanol, polyester-8, polyglyceryl-4 isostearate, polymethyl methacrylate, polymethylsilsequioxane, tocopherol